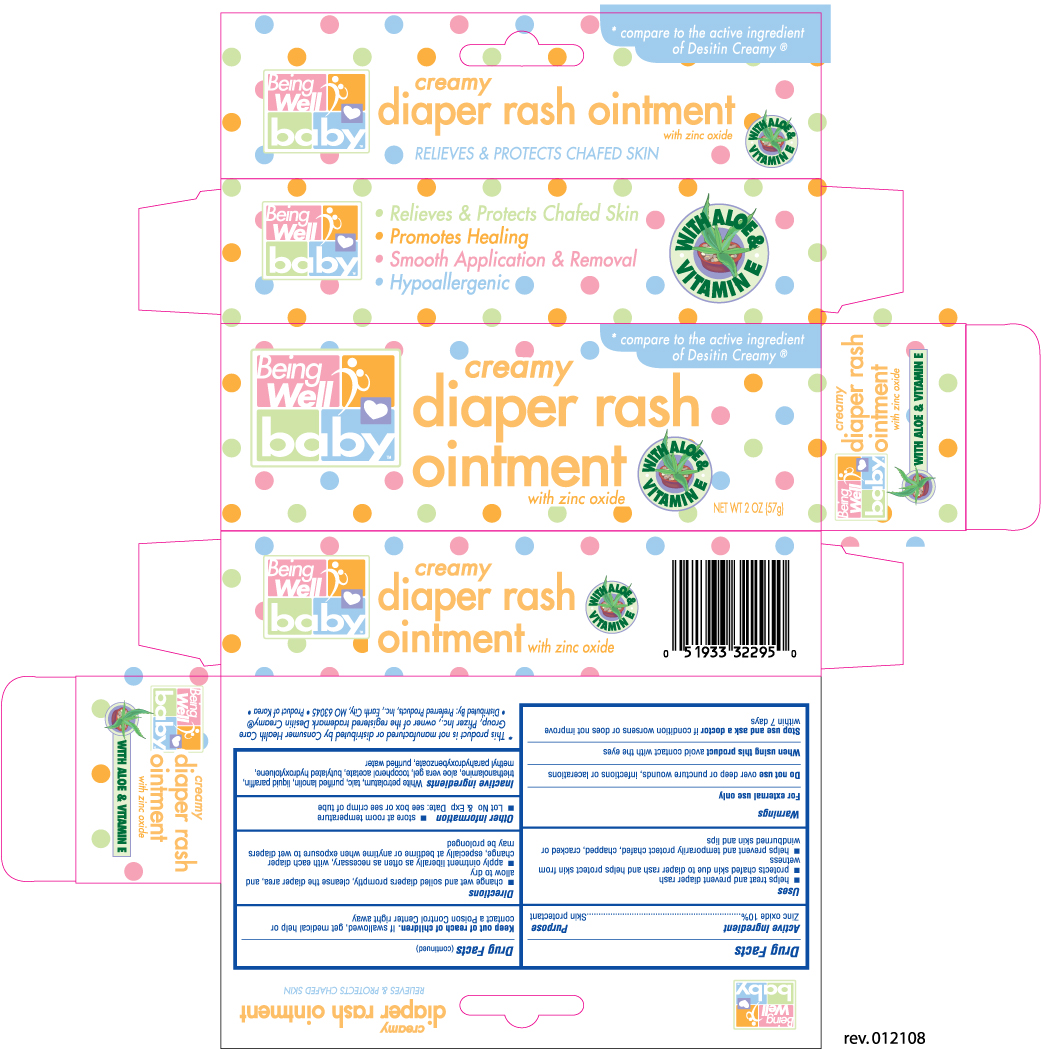 DRUG LABEL: BEING WELL DIAPER RASH CREAMY
NDC: 68169-3229 | Form: OINTMENT
Manufacturer: TAI GUK PHARM. CO., LTD.
Category: otc | Type: HUMAN OTC DRUG LABEL
Date: 20101117

ACTIVE INGREDIENTS: ZINC OXIDE 0.10 g/1 g
INACTIVE INGREDIENTS: PETROLATUM; TALC; LANOLIN; MINERAL OIL; TROLAMINE; ALOE VERA LEAF; WATER

Drug Facts

Active Ingredient Purpose

Zinc oxide 10% ........................................................................ Skin protectant

Uses

- helps treat and prevent diaper rash
- protects chafed skin due to diaper rash and helps protect skin from wetness
- helps prevent and temporarily protect chafed, chapped, cracked or windburned skin and lips

Warnings

For external use only

Do not use over deep or puncture wounds, infections or lacerations

When using this product avoid contact with the eyes

Stop use and ask a doctor if condition worsens or does not improve within 7 days

Keep out of reach of children. If swallowed, get medical help or contact a Poison Control Center right away

Directions

- change wet and soiled diapers promptly, cleanse the diaper area and allow to dry
- apply ointment liberally as often as necessary, with each diaper change, especially at bedtime or anytime when exposure to wet diapers may be prolonged

Other information

- store at room temperature
- Lot No and Exp. Date: see box or see crimp of tube

Inactive ingredients

White petrolatum, talc, purified lanolin, liquid paraffin, triethanolamine, aloe vera gel, tocopherol acetate, butylated hydroxyloluene, methyl parahydroxybenzoate, purified water

DOSAGE AND ADMINISTRATION

Distributed by: Preferred Products, Inc.

Earth City, MO 63045

Product of Korea

PACKAGE LABEL

Enter section text here